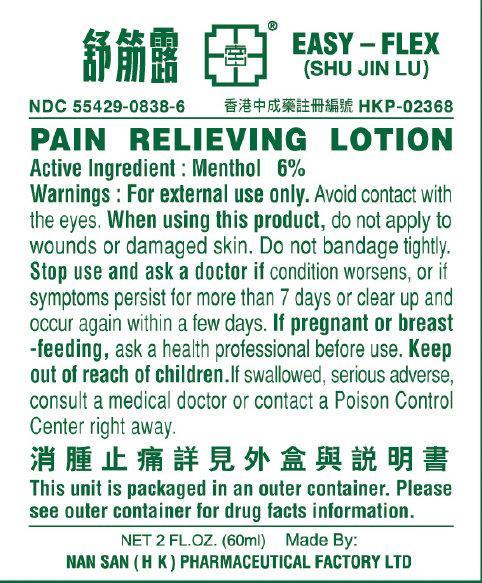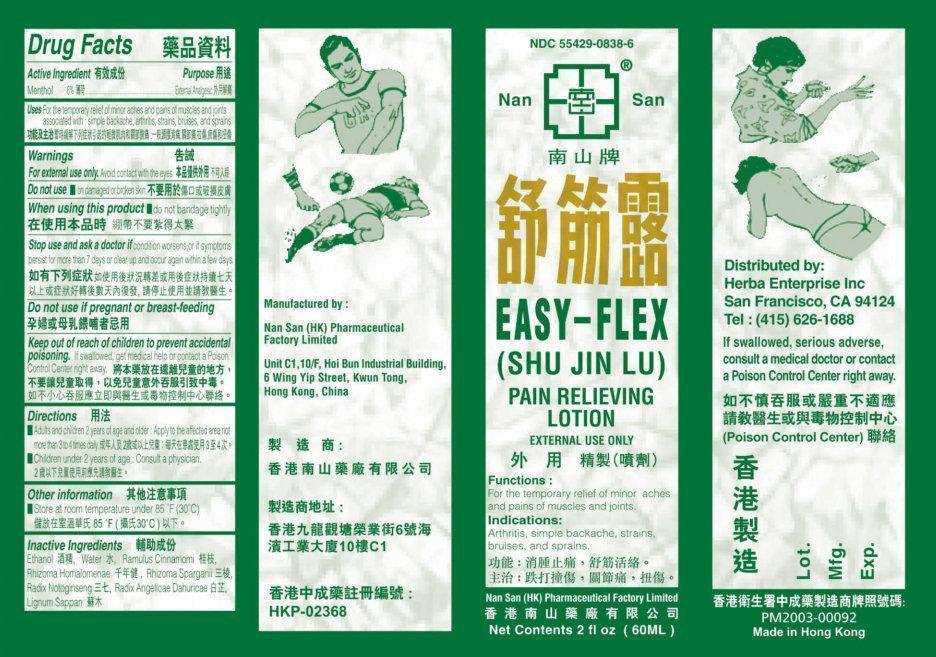 DRUG LABEL: Nan San EASY FLEX Pain Relieving
NDC: 55429-0838 | Form: LOTION
Manufacturer: Herba Enterprise Inc
Category: otc | Type: HUMAN OTC DRUG LABEL
Date: 20140618

ACTIVE INGREDIENTS: MENTHOL 60 mg/1 mL
INACTIVE INGREDIENTS: ALCOHOL; WATER; ANGELICA DAHURICA VAR. FORMOSANA WHOLE

Nan San EASY-FLEX Pain Relieving Lotion

Active Ingredients

Menthol 6%

Purpose

External Analgesic

Uses

For the temporary relief of minor aches and pains of muscles and joints associated with: simple backache, arthritis, strains, bruises, and sprains.

Warnings

For external use only.

Avoid contact with the eyes.

Do not use

- on damaged or broken skin

When using this product

- do not bandage tightly

Stop use and ask a doctor if

condition worsens, or if symptoms persist for more than 7 days or clear up and occur again within a few days.

Keep out of reach of children to prevent accidental poisoning.

If swallowed, get medical help or contact a Poison Control Center right away.

Directions

- Adults and children 2 years of age and older: Apply to the affected area not more than 3 to 4 times daily
- Children under 2 years of age: Consult a physician

Other Information

- Store at room temperature under 85 degrees F (30 degrees C)

Inactive Ingredients

Ethanol, Water, Ramulus Cinnamomi, Rhizoma Homalomenae, Rhizoma Sparganii, Radix Notoginseng, Radix Angelicae Dahurica, Lignum Sappan

Manufactured By:

Nan San (HK) Pharmaceutical Factory Limited

Unit C1, 10/f, Hoi Bun Industrial Building, 6 Wing Yip Street,

Kwun Tong, Hong Kong, China.

Distributed By:

Herba Enterprise Inc

San Francisco, CA 94124

Tel: (415) 626-1688